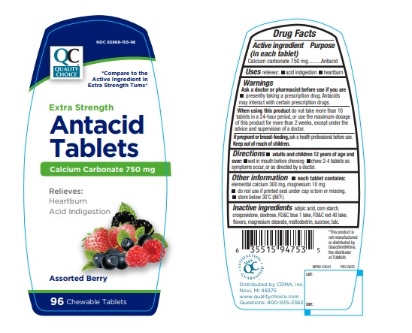 DRUG LABEL: Quality Choice Extra Strength Assorted Berry  Antacid
NDC: 63868-155 | Form: TABLET, CHEWABLE
Manufacturer: Chain Drug Marketing Association Inc.
Category: otc | Type: Human OTC Drug Label
Date: 20241218

ACTIVE INGREDIENTS: CALCIUM CARBONATE 750 mg/1 1
INACTIVE INGREDIENTS: STARCH, CORN; DEXTROSE, UNSPECIFIED FORM; MAGNESIUM STEARATE; MALTODEXTRIN; SUCROSE; TALC; CROSPOVIDONE; ADIPIC ACID; FD&C BLUE NO. 1; FD&C RED NO. 40

QC Extra Strength Antacid Assorted Berry

ACTIVE INGREDIENT (in each tablet)

Calcium carbonate 750 mg

PURPOSE

Antacid

USE(S)

relieves:

- acid indigestion
- heartburn

WARNINGS

.

ASK A DOCTOR OR PHARMACIST BEFORE USE IF YOU ARE

- presently taking a prescription drug. Antacids may interact with certain prescription drugs.

WHEN USING THIS PRODUCT

do not take more than 10 tablets in a 24-hour period, or use the maximum dosage of this product for more than 2 weeks, except under the advice and supervision of a doctor.

IF PREGNANT OR/BREASTFEEDING,

ask a health professional before use.

KEEP OUT OF REACH OF CHILDREN

.

DIRECTIONS

- adults and children 12 years of age and over:
- wet in mouth before chewing
- chew 2-4 tablets as symptoms occur, or as directed by a doctor.

OTHER INFORMATION

- each tablet contains: elemental calcium 300 mg, magnesium 10mg
- do not use if printed seal under cap is torn or missing.
- store below 30°C (86°F).

INACTIVE INGREDIENTS

adipic acid, corn starch, crospovidone, dextrose, FD&C blue 1 lake, FD&C red 40 lake, flavors, magnesium stearate, maltodextrin, sucrose, talc.

PRINCIPAL DISPLAY PANEL

NDC 63868-155-96

QC

QUALITY CHOICE

*Compare to the Active Ingredient in Extra Strength TUMS®

Extra Strength
Antacid Tablets

Calcium Carbonate 750mg

RELIEVES:

Heartburn

Acid Indigestion

Assorted Berry

96 Chewable Tablets